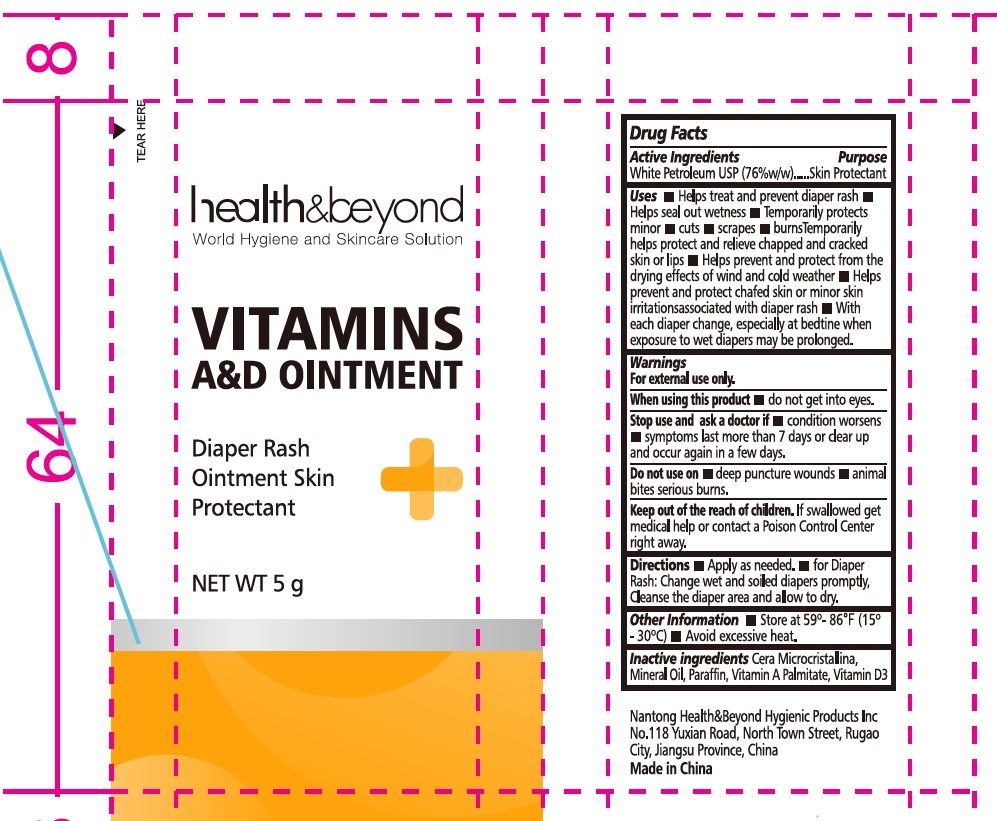 DRUG LABEL: health beyond VITAMINS AD
NDC: 43473-091 | Form: OINTMENT
Manufacturer: Nantong Health & Beyond Hygienic Products Inc.
Category: otc | Type: HUMAN OTC DRUG LABEL
Date: 20251123

ACTIVE INGREDIENTS: PETROLATUM 76 g/100 g
INACTIVE INGREDIENTS: MINERAL OIL; MICROCRYSTALLINE WAX; PARAFFIN; VITAMIN A PALMITATE; VITAMIN D

43473-091, Health Beyond VITAMINS AD Ointment

Active ingredient

White Petroletum USP, 76% w/w

Purpose

Skin Protectant

Uses

- Helps treat and prevent diaper rash
- Helps seal out wetness
- Temporarily protects minor cuts, scrapes, burns
- Temporarily helps protect and relieve chapped and cracked skin or lips
- Helps prevent and protect from the drying effects of winds and cold weather
- Helps prevent and protect chafed skin or minor skin irritations associated with diaper rash
- With each diaper change, especially at bedtime when exposure to wet diapers may be prolonged

Warnings

For external use only
When using this product

- Do not get into eyes

Stop use and ask a doctor if

- Condition worsens
- Symptoms last more than 7 days or clear up and occur again in a few days

Do not use on

- Deep puncture wounds
- Animal bites
- Serious burns

Keep out of reach of children. If swallowed, get medical help or contact a Poison Control Center right away

Directions

- Apply as needed
- For diaper rash: Change wet and soiled diapers promptly. Cleanse the diaper area and allow to dry

Other information

- Store at 59-86F (15-30C)
- Avoid excessive heat

Inactive ingredients

Cera Microcrystalline, Mineral Oil, Paraffin, Vitamin A, Vitamin A Palmitate, Vitamin D3